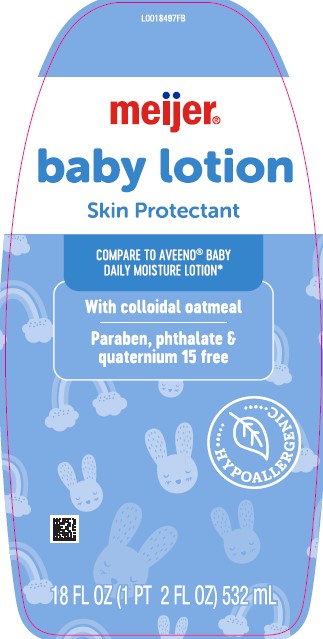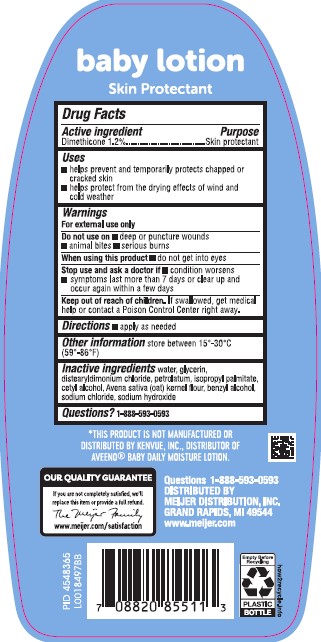 DRUG LABEL: Dimethicone
NDC: 79481-0496 | Form: LOTION
Manufacturer: Meijer, Inc.
Category: otc | Type: HUMAN OTC DRUG LABEL
Date: 20260219

ACTIVE INGREDIENTS: DIMETHICONE 12 mg/1 mL
INACTIVE INGREDIENTS: WATER; GLYCERIN; DISTEARYLDIMONIUM CHLORIDE; PETROLATUM; ISOPROPYL PALMITATE; CETYL ALCOHOL; OATMEAL; BENZYL ALCOHOL; SODIUM CHLORIDE; SODIUM HYDROXIDE

Meijer 496.000/496AA
Daily Baby Lotion with Colloidal Oatmeal

Claims

baby lotion

Skin Protectant

Active ingredient

Dimethicone 1.2%

Purpose

Skin protectant

Uses

- helps prevent and temporarily protects chapped or cracked skin
- helps protect from the drying effects of wind and cold weather

Warnings

For external use only

Do not use on

- deep or punture wounds
- animal bites
- serious burns

When using this product

do not get into eyes

Stop use and ask a doctor if

- condition worsens
- symptoms last more than 7 days or clear up and occur again within a few days

Keep out of reach of children.

If swallowed, get medical help or contact Poison Control right away.

Directions

- apply as needed

Other information

store between 15°-30°C (59°-86°F)

inactive ingredients

water, glycerin, distearyldimonium chloride, petrolatum, isopropyl palmitate, cetyl alcohol, Avena sativa (oat) kernel flour, benzyl alcohol, sodium chloride, sodium hydroxide

Questions?

1-888-593-0593

Disclaimer

*This product is not manufactured or distributed by Kenvue, Inc., distributor of AveenoBaby Daily Moisture Lotion.

Adverse reaction

OUR QUALITY GUARANTEE

If you are not completely satisfied, we'll replace this item or provide a full refund.

The Meijer Family

www.meijer.com/satisfaction

Questions 1-888-593-0593

DISTRIBUTED BY

MEIJER DISTRIBUTION, INC.

GRAND RAPIDS, MI 49544

www.meijer.com

Empty Before Recycling

PLASTIC BOTTLE

how2recycle.info

Principal panel display

meijer®

baby lotion

Skin Protectant

COMPARE TO AVEENO®BABY DAILY LOTION*

With colloidal oatmeal

Paraben, phthalate & quaternium 15 free

HYPOALLERGENIC

18 FL OZ (1 PT 2 FL OZ) 532 mL